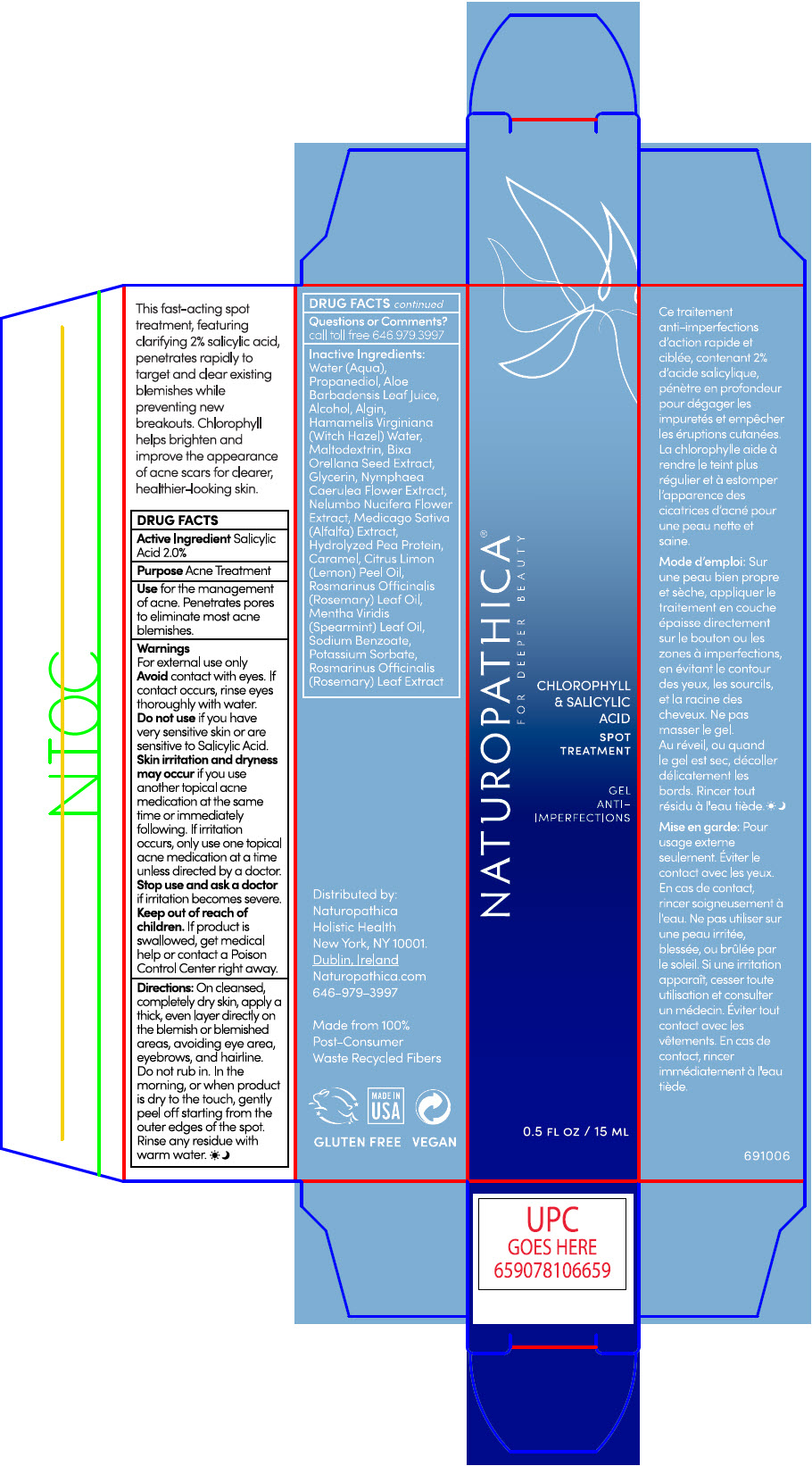 DRUG LABEL: NATUROPATHICA CHLOROPHYLL AND SALICYLIC ACID SPOT TREATMENT
NDC: 64657-002 | Form: GEL
Manufacturer: Naturopathica Holistic Health
Category: otc | Type: HUMAN OTC DRUG LABEL
Date: 20240530

ACTIVE INGREDIENTS: SALICYLIC ACID 2 g/100 mL
INACTIVE INGREDIENTS: WATER; PROPANEDIOL; ALOE VERA LEAF; ALCOHOL; SODIUM ALGINATE; HAMAMELIS VIRGINIANA TOP WATER; MALTODEXTRIN; BIXA ORELLANA SEED; GLYCERIN; NYMPHAEA CAERULEA FLOWER; NELUMBO NUCIFERA FLOWER; MEDICAGO SATIVA WHOLE; CARAMEL; LEMON OIL, COLD PRESSED; ROSEMARY OIL; SPEARMINT OIL; SODIUM BENZOATE; POTASSIUM SORBATE; ROSEMARY

NATUROPATHICA®CHLOROPHYLL AND SALICYLIC ACID SPOT TREATMENT

ACTIVE INGREDIENTS

SALICYLIC ACID 2.0%

PURPOSE

ACNE TREATMENT

Use

for the management of acne.

Penetrates pores to eliminate most acne blemishes.

Warnings

For external use only

When using this product

- Avoid contact with eyes. If contact occurs, rinse eyes thoroughly with water.
- Do not use if you have very sensitive skin or are sensitive to Salicylic Acid.
- skin irritation and dryness may occur if you use another topical acne medication at the same time or immediately following. If irritation occurs, only use one topical acne medication at a time unless directed by a doctor.

Stop use and ask a doctor

If irritation becomes severe.

Keep out of reach of children.

If swallowed, get medical help or contact a Poison Control Center right away.

Directions

On cleansed, completely dry skin, apply a thick, even layer directly on the blemish or blemished areas avoiding eye area, eyebrows, and hairline. Do not rub in. IN the morning or when product is dry to the touch, gently peel off starting from the outer edges of the spot. Rinse any residue with warm water.

Questions or comments?

Call toll free 646.979.3997

INACTIVE INGREDIENTS

WATER (AQUA), PROPANEDIOL, ALOE BARBADENSIS LEAF JUICE,ALCOHOL, ALGIN, HAMAMELIS VIRGINIANA (WITCH HAZEL) WATER, MALTODEXTRIN, BIXA ORELLANA SEED EXTRACT, GLYCERIN, NYMPHAEA CAERULEA FLOWER EXTRACT, NELUMBO NUCIFERA FLOWER EXTRACT, MEDICAGO SATIVA (ALFALFA) EXTRACT, HYDROLYZED PEA PROTEIN, CARAMEL, CITRUS LIMON (LEMON) PEEL OIL, ROSMARINUS OFFICINALIS (ROSEMARY) LEAF OIL, MENTHA VIRIDIS (SPEARMINT) LEAF OIL, SODIUM BENZOATE, POTASSIUM SORBATE, ROSMARINUS OFFICINALIS (ROSEMARY) LEAF EXTRACT.

CERTIFIED ORGANIC

Distributed by:
Naturopathica
Holistic Health
New York, NY 10001.
Dublin, Ireland

PRINCIPAL DISPLAY PANEL - 15 ML Tube Carton

NATUROPATHICA®
FOR DEEPER BEAUTY

CHLOROPHYLL
& SALICYLIC
ACID

SPOT
TREATMENT

GEL
ANTI-
IMPERFECTIONS

0.5 FL OZ / 15 ML